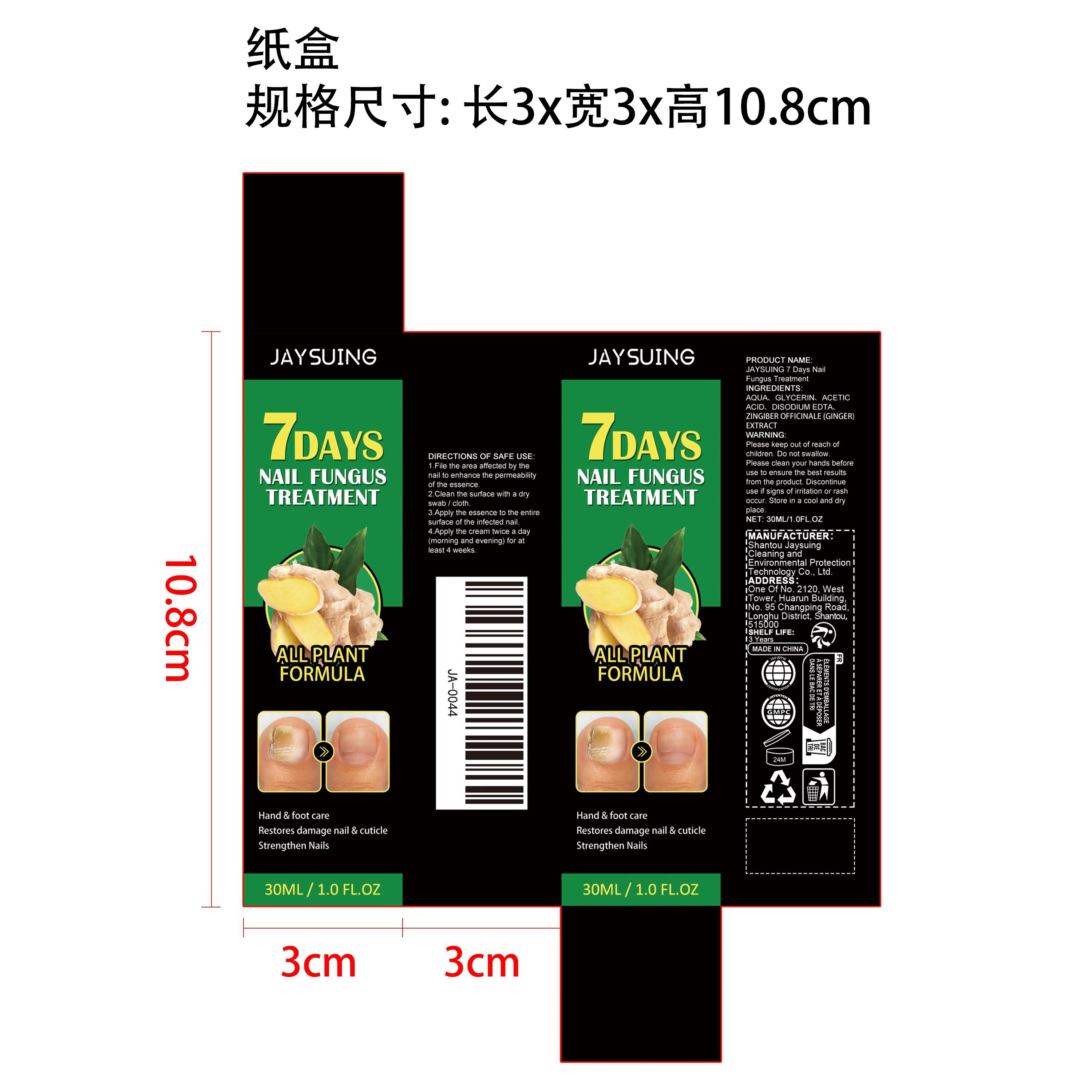 DRUG LABEL: JAYSUING 7 Days Nail Fungus Treatment
NDC: 85060-003 | Form: LIQUID
Manufacturer: Shantou Jaysuing Cleaning and Environmental Protection Technology Co., Ltd.
Category: otc | Type: HUMAN OTC DRUG LABEL
Date: 20251127

ACTIVE INGREDIENTS: ZINGIBER OFFICINALE (GINGER) ROOT OIL 0.006 mg/30 mg
INACTIVE INGREDIENTS: GLYCERIN 1.5 mg/30 mg; EDETATE DISODIUM 0.03 mg/30 mg; AQUA 22.464 mg/30 mg; ACETIC ACID 6 mg/30 mg

ACTIVE INGREDIENT

ZINGIBER OFFICINALE (GINGER) ROOT OIL

PURPOSE

Hand & foot care
Restores damage nail & cuticle
Strengthen Nails

WHEN USING

1.File the area affected by the nail to enhance the permeability of the essence.

2.Clean the surface with a dry swab / cloth.

3.Apply the essence to the entire surface of the infected nail.

4.Apply the cream twice a day (morning and evening) for at least 4 weeks.

WARNINGS

Please keep out of reach of children. Do not swallow.Please clean your hands before use to ensure the best results from the product. Discontinue use if signs of irritation or rash occur. Store in a cool and dry place.

STOP USE

Discontinue use if signs of irritation or rash occur.

DO NOT USE

Discontinue use if signs of irritation or rash occur.

INACTIVE INGREDIENT

AQUA,
GLYCERIN、
ACETIC ACID、

EDETATE DISODIUM

KEEP OUT OF REACH OF CHILDREN

Please keep out of reach of children. Do not swallow.

STORAGE AND HANDLING

Store in a cool and dry place.